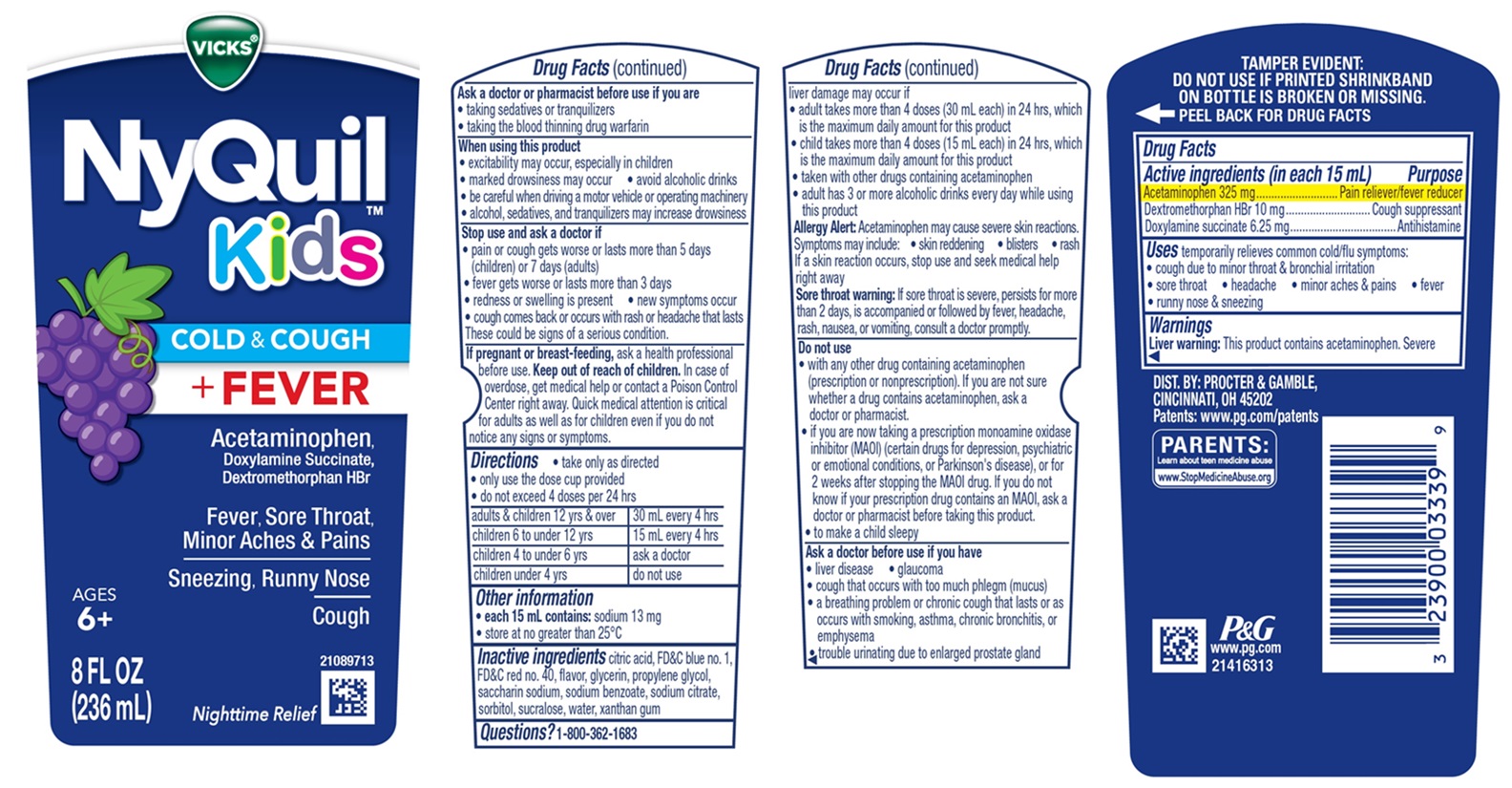 DRUG LABEL: Vicks NyQuil Kids
NDC: 84126-305 | Form: LIQUID
Manufacturer: The Procter & Gamble Manufacturing Company
Category: otc | Type: HUMAN OTC DRUG LABEL
Date: 20251202

ACTIVE INGREDIENTS: ACETAMINOPHEN 325 mg/15 mL; DEXTROMETHORPHAN HYDROBROMIDE 10 mg/15 mL; DOXYLAMINE SUCCINATE 6.25 mg/15 mL
INACTIVE INGREDIENTS: FD&C BLUE NO. 1; FD&C RED NO. 40; PROPYLENE GLYCOL; WATER; SACCHARIN SODIUM; SODIUM BENZOATE; SUCRALOSE; SORBITOL; XANTHAN GUM; GLYCERIN; TRISODIUM CITRATE DIHYDRATE; ANHYDROUS CITRIC ACID

VICKS®NyQuil™ Kids COLD & COUGH + FEVER

Drug Facts

Active ingredients (in each 15 mL)

Acetaminophen 325 mg

Dextromethorphan HBr 10 mg

Doxylamine succinate 6.25 mg

Purpose

Pain reliever/fever reducer

Cough suppressant

Antihistamine

Uses

temporarily relieves common cold/flu symptoms:
• cough due to minor throat & bronchial irritation
• sore throat • headache • minor aches & pains • fever
• runny nose & sneezing

Warnings

Liver warning:

This product contains acetaminophen.
Severe liver damage may occur if

- adult takes more than 4 doses (30 mL each) in 24 hrs, which is the maximum daily amount for this product
- child takes more than 4 doses (15 mL each) in 24 hrs, which is the maximum daily amount for this product
- taken with other drugs containing acetaminophen
- adult has 3 or more alcoholic drinks every day while using this product

Allergy Alert:

Acetaminophen may cause severe skin reactions.
Symptoms may include:

- Skin reddening
- Blisters
- Rash

If a skin reaction occurs, stop use and seek medical help right away

Sore throat warning:

If sore throat is severe, persists for more than 2 days, is accompanied or followed by fever, headache, rash, nausea, or vomiting, consult a doctor promptly.

Do not use

- with any other drug containing acetaminophen (prescription or nonprescription). If you are not sure whether a drug contains acetaminophen, ask a doctor or pharmacist.
- if you are now taking a prescription monoamine oxidase inhibitor (MAOI) (certain drugs for depression, psychiatric or emotional conditions, or Parkinson's disease), or for 2 weeks after stopping the MAOI drug. If you do not know if your prescription drug contains an MAOI, ask a doctor or pharmacist before taking this product.
- to make a child sleepy

Ask a doctor before use if you have

- liver disease
- glaucoma
- cough that occurs with too much phlegm (mucus)
- a breathing problem or chronic cough that lasts or as occurs with smoking, asthma, chronic bronchitis or emphysema
- trouble urinating due to enlarged prostate gland

Ask a doctor or pharmacist before use if you are

- taking sedatives or tranquilizers
- taking the blood thinning drug warfarin

When using this product

- excitability may occur, especially in children
- marked drowsiness may occur
- avoid alcoholic drinks
- be careful when driving a motor vehicle or operating machinery
- alcohol, sedatives, and tranquilizers may increase drowsiness

Stop use and ask a doctor if

- pain or cough gets worse or lasts more than 5 days (children) or 7 days (adults)
- fever gets worse or lasts more than 3 days
- redness or swelling is present
- new symptoms occur
- cough comes back or occurs with rash or headache that lasts

These could be signs of a serious condition.

PREGNANCY OR BREAST FEEDING

If pregnant or breast-feeding, ask a health professional before use.

OVERDOSAGE

In case of overdose, get medical help or contact a Poison Control Center right away. Quick medical attention is critical for adults as well as for children even if you do not notice any signs or symptoms.

Directions

- take only as directed
- only use the dose cup provided
- do not exceed 4 doses per 24 hrs

adults & children 12 yrs & over | 30 mL every 4 hrs
children 6 to under 12 yrs | 15 mL every 4 hrs
children 4 to under 6 yrs | ask a doctor
children under 4 yrs | do not use

Other information

- each 15 mL contains:sodium 13 mg
- store at no greater than 25°C

Inactive ingredients

citric acid, FD&C blue no. 1, FD&C red no. 40, flavor, glycerin, propylene glycol, saccharin sodium, sodium benzoate, sodium citrate, sorbitol, sucralose, water, xanthan gum

Questions?

1-800-362-1683

TAMPER EVIDENT: DO NOT USE IF PRINTED SHRINKBAND ON BOTTLE IS BROKEN OR MISSING.

DIST. BY:

PROCTER & GAMBLE

CINCINNATI, OH 45202

PRINCIPAL DISPLAY PANEL - 236 ml Bottle Label

VICKS®

NyQuil ™

Kids

COLD & COUGH

+ FEVER

Acetaminophen, Doxylamine Succinate, Dextromethorphan HBr

Fever, Sore Throat, Minor Aches & Pains

Sneezing, Runny Nose

Cough

AGES 6+

Nighttime Relief

8 FL OZ (236 mL)